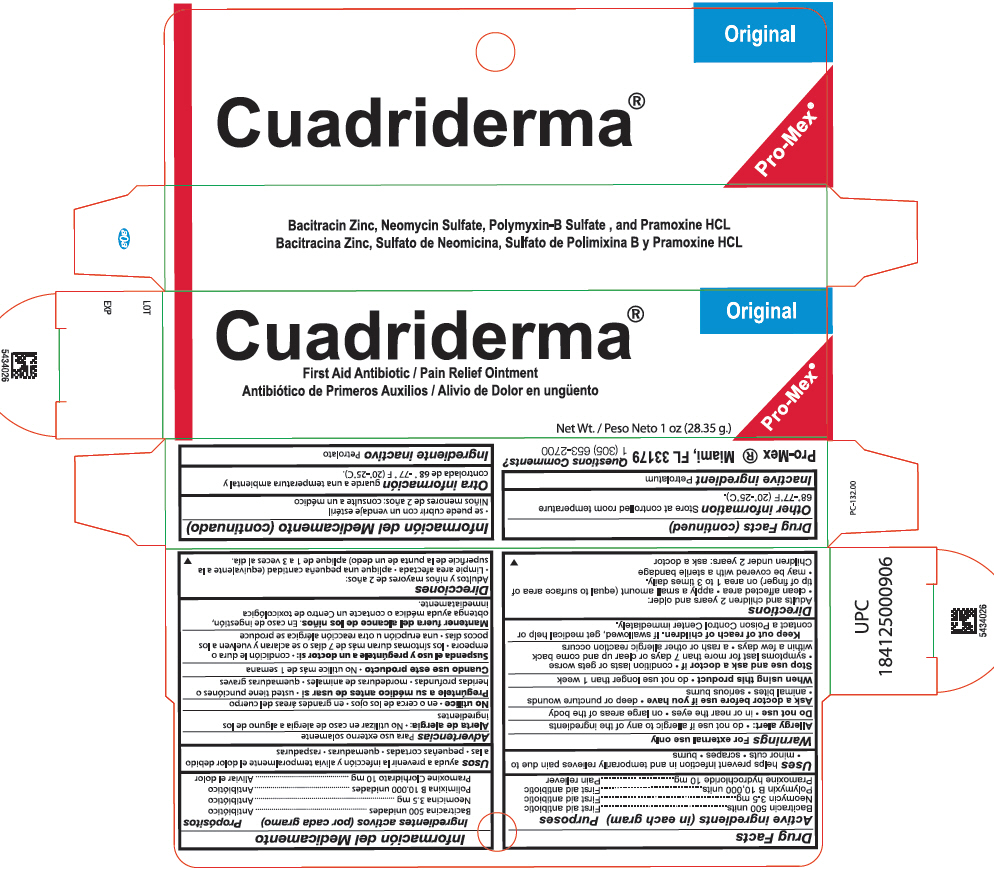 DRUG LABEL: Cuadriderma
NDC: 58988-1170 | Form: OINTMENT
Manufacturer: ProMex LLC
Category: otc | Type: HUMAN OTC DRUG LABEL
Date: 20220125

ACTIVE INGREDIENTS: Bacitracin Zinc 500 [iU]/1 g; Polymyxin B Sulfate 10000 [iU]/1 g; Neomycin Sulfate 3.5 mg/1 g; PRAMOXINE HYDROCHLORIDE 10 mg/1 g
INACTIVE INGREDIENTS: Petrolatum

Cuadriderma®

Drug Facts

ACTIVE INGREDIENT

Active ingredients (in each gram) | Purpose
Bacitracin 500 units | First aid antibiotic
Neomycin 3.5 mg | First aid antibiotic
Polymyxin B 10,000 units | First aid antibiotic
Pramoxine hydrochloride 10 mg | Pain reliever

Uses

helps prevent infection in and temporarily relieves pain due to

- minor cuts
- scrapes
- burns

Warnings

For external use only

Allergy alert

- do not use if allergic to any of the ingredients

Do not use

- in or near the eyes
- on large areas of the body

Ask a doctor before use if you have

- deep or puncture wounds
- animal bites
- serious burns

When using this product

- do not use longer than 1 week

Stop use and ask a doctor if

- condition lasts or gets worse
- symptoms last for more than 7 days or clear up and come back within a few days
- a rash or other allergic reaction occurs.

Keep out of reach of children. If swallowed, get medical help or contact a Poison Control Center immediately.

Directions

Adults and children 2 years and older:

- clean affected area
- apply a small amount (equal to surface area of tip of finger) on area 1 to 3 times daily.
- may be covered with sterile bandage.

Children under 2 years: ask a doctor

Other information

Store at controlled room temperature 68°-77°F (20°-25°C)

Inactive ingredient

Petrolatum

Questions Comments

1 (305) 653-2700

PRINCIPAL DISPLAY PANEL - 28.35 g Tube Carton

Original

Cuadriderma®
First Aid Antibiotic / Pain Relief Ointment

Net Wt. 1 oz (28.35 g.)

Pro-Mex®